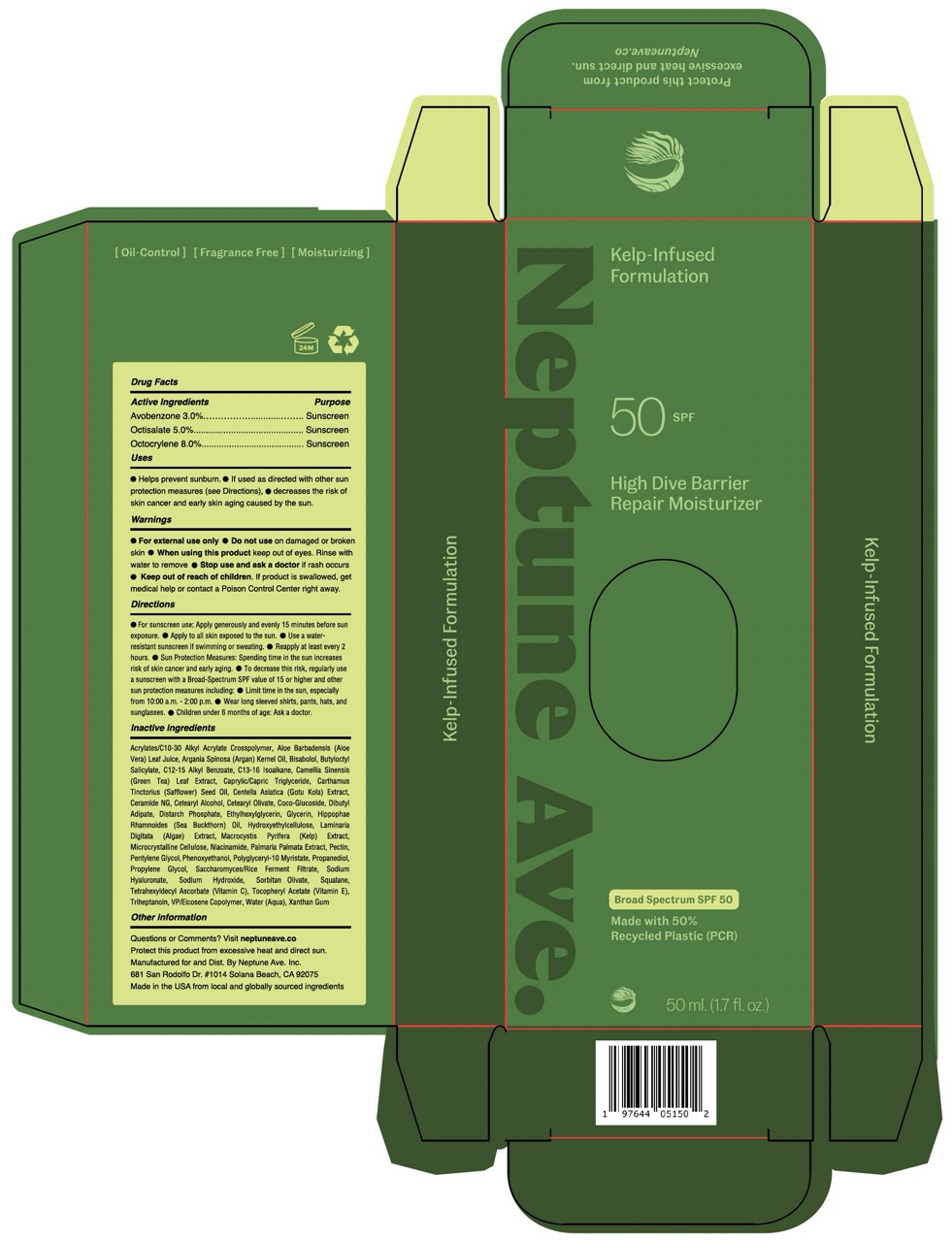 DRUG LABEL: Neptune Ave. High Dive Barrier Repair Moisturizer Broad Spectrum SPF 50
NDC: 84869-000 | Form: CREAM
Manufacturer: Neptune Ave. Inc.
Category: otc | Type: HUMAN OTC DRUG LABEL
Date: 20250122

ACTIVE INGREDIENTS: OCTOCRYLENE 8 g/100 g; AVOBENZONE 3 g/100 g; OCTISALATE 5 g/100 g
INACTIVE INGREDIENTS: WATER; CAPRYLIC/CAPRIC TRIGLYCERIDE; PHENOXYETHANOL; NIACINAMIDE; COCO-GLUCOSIDE; PALMARIA PALMATA; LAMINARIA DIGITATA; MACROCYSTIS PYRIFERA (KELP); CARTHAMUS TINCTORIUS (SAFFLOWER) SEED OIL; BISABOLOL; ACRYLATES/C10-30 ALKYL ACRYLATE CROSSPOLYMER (60000 MPA.S); HYDROXYETHYLCELLULOSE; CETEARYL ALCOHOL; HIPPOPHAE RHAMNOIDES SEED OIL; PECTIN; CERAMIDE NG; PROPYLENE GLYCOL; RICE GERM; SODIUM HYALURONATE; DISTARCH PHOSPHATE, CORN; PENTYLENE GLYCOL; SQUALANE; C13-16 ISOPARAFFIN; ARGANIA SPINOSA KERNEL OIL; DIBUTYL ADIPATE; ETHYLHEXYLGLYCERIN; MICROCRYSTALLINE CELLULOSE; BUTYLOCTYL SALICYLATE; POLYGLYCERYL-10 MYRISTATE; CETEARYL OLIVATE; SACCHAROMYCES LYSATE; EICOSYL POVIDONE; TRIHEPTANOIN; GREEN TEA LEAF; CENTELLA ASIATICA LEAF; .ALPHA.-TOCOPHEROL ACETATE, DL-; TETRAHEXYLDECYL ASCORBATE; XANTHAN GUM; GLYCERIN; SODIUM HYDROXIDE; SORBITAN OLIVATE; C12-15 ALKYL BENZOATE; ALOE BARBADENSIS LEAF JUICE; PROPANEDIOL

Neptune Ave. High Dive Barrier Repair Moisturizer Broad Spectrum SPF 50 (50 ml / 1.7 fl oz)

Active Ingredients

Avobenzone 3%
Octisalate 5%
Octocrylene 8%

Purpose

Sunscreen

Uses

• Helps prevent sunburn. • If used as directed, with other sun protection measures (see Directions), decreases the risk of skin cancer and early skin aging caused by the sun.

Warnings

For external use only

Do not use

on damaged or broken skin

When using this product

keep out of eyes. Rinse with water to remove.

Stop use and ask a doctor if

rash occurs.

Keep out of reach of children

If product is swallowed, get medical help or contact a Poison Control Center right away.

Directions

• For sunscreen use: Apply generously and evenly every 15 minutes before sun exposure. • Apply to all skin exposed to the sun. • Use a water-resistant sunscreen if swimming or sweating. • Reapply at least every 2 hours. • Sun Protection Measures: Spending time in the sun increases risk of skin cancer and early aging. • To decrease this risk, regularly use a sunscreen with a Broad Spectrum SPF value of 15 or higher and other sun protection measures including: • Limit time in the sun, especially from 10:00 a.m. - 2:00 p.m. • Wear long sleeved shirts, pants, hats, and sunglasses. • Children under 6 months of age: Ask a doctor.

Other information

Protect this product from excessive heat and direct sun.

Inactive ingredients

Water (Aqua), Aloe Barbadensis (Aloe Vera) Leaf Juice, Butyloctyl Salicylate, Polyglyceryl-10 Myristate, Distarch Phosphate, Propanediol, Sorbitan Olivate, Cetearyl Olivate, Microcrystalline Cellulose, Diburyl Adipate, Caprylic/Capric Triglyceride, C12-15 Alkyl Benzoate, Phenoxyethanol, Argania Spinosa (Argan) Kernel Oil, Cetearyl Alcohol, Tocopheryl Acetate (Vitamin E), Pentylene Glycol, Niacinamide, VP/Eicosene Copolymer, Coco-Glucoside, Pectin. Triheptanoin, Squalane, Acrylates/C10-30 Alkyl Acrylate Crosspolymer, Centella Asiatica (Gotu Kola) Extract, Ceramide NG, C13-16 Isoalkane, Propylene Glycol, Saccharomyces/Rice Ferment Filtrate, Carthamus Tinctorius (Safflower) Seed Oil, Tetrahexyldecyl Ascorbate (Vitamin C), Hippophae Rhamnoides (Sea Buckthorn) Oil, Ethylhexylglycerin, Hydroxyethylcellulose,, Xanthan Gum, Glycerin, Bisabolol, Camellia Sinensis (Green Tea) Leaf Extract, Macrocystis Pyrifera (Kelp) Extract, Palmaria Palmata Extract, Laminaria Digitata (Algae) Extract, Sodium Hydroxide, Sodium Hyaluronate.

Questions?

Visit neptuneave.co

Principal Display Panel

Neptune Ave.

Kelp-Infused
Formulation

50 SPF

High Dive Barrier
Repair Moisturizer

Broad Spectrum SPF 50
Made with 50%
Recycled Plastic (PCR)

50 ml (1.7 fl oz)